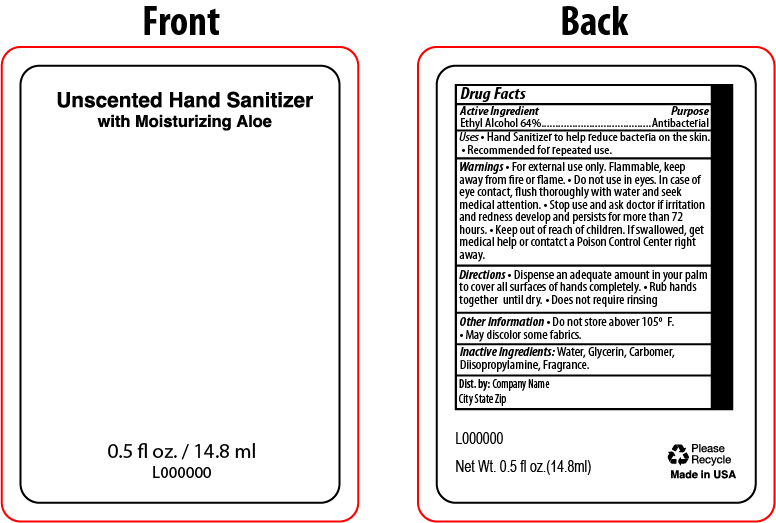 DRUG LABEL: Hand Sanitizer
NDC: 65692-2073 | Form: GEL
Manufacturer: Raining Rose
Category: otc | Type: HUMAN OTC DRUG LABEL
Date: 20220310

ACTIVE INGREDIENTS: ALCOHOL 64 mL/100 mL
INACTIVE INGREDIENTS: CARBOMER INTERPOLYMER TYPE A (ALLYL SUCROSE CROSSLINKED); WATER; DIISOPROPYLAMINE; GLYCERIN

Hand Sanitizer 0.5 fl oz Square Bottle 64%

Active Ingredient

Ethyl Alcohol 64%

PURPOSE

Antibacterial

INDICATIONS AND USAGE

Uses - Hand Sanitizer to help reduce bacteria on the skin. - Recommended for repeated use.

WARNINGS

- For external use only. Flammable, keep away from fire or Flame. - Do not use in eyes. In case of eye contact, flush throroughly with water and seek medical attention. -Stop use and ask doctor if irritation and redness develop and persists for more than 72 hours.

Keep out of reach of children. If swallowed, get medical help or contact a Poison Control Center right away.

Directions

- Dispense an adequate amount in your palm to cover all surfaces of hands completely
- Rub hands together until dry
- Does not require rinsing

OTHER SAFETY INFORMATION

- Do not store above 105 °F
- May discolor some fabrics

INACTIVE INGREDIENT

Water, Glycerin, Carbomer, Diisopropylamine, Fragrance